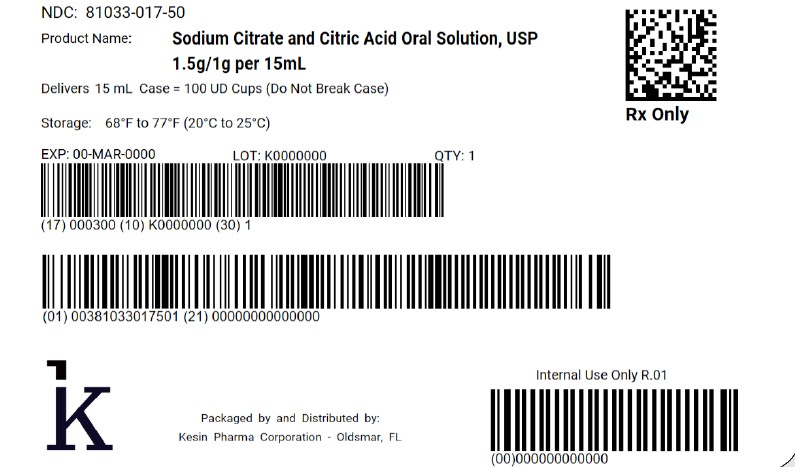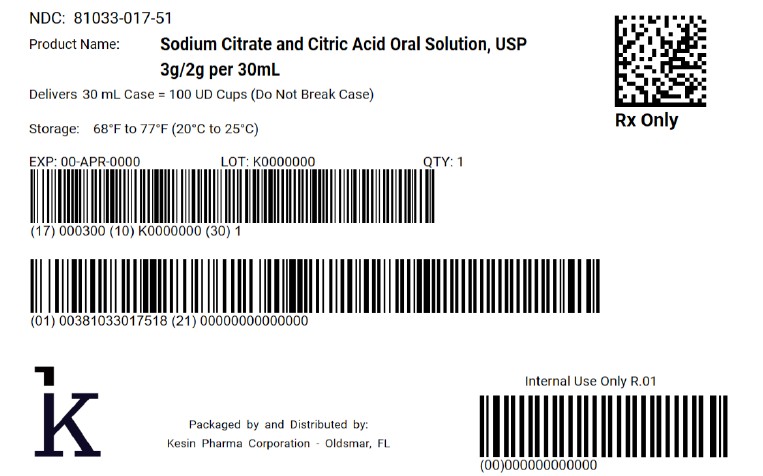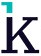 DRUG LABEL: Sodium Citrate and Citric Acid
NDC: 81033-017 | Form: SOLUTION
Manufacturer: Kesin Pharma Corporation
Category: prescription | Type: HUMAN PRESCRIPTION DRUG LABEL
Date: 20250421

ACTIVE INGREDIENTS: ANHYDROUS CITRIC ACID 334 mg/5 mL; SODIUM CITRATE 500 mg/5 mL

Sodium Citrate and Ctric Acid Oral Solution, USP

DESCRIPTION

Sodium Citrate and Citric Acid Oral Solution, USP is a stable and pleasant-tasting systemic alkalizer containing sodium citrate and citric acid in a sugar-free base. It is a non-particulate neutralizing buffer.
Sodium Citrate and Citric Acid Oral Solution, USP contains in each teaspoonful (5 mL):
SODIUM CITRATE Dihydrate 500 mg (0.34 Molar)
CITRIC ACID Monohydrate 334 mg (0.32 Molar)
Each mL contains 1 mEq sodium ion and is equivalent to 1 mEq bicarbonate (HCO3).
INACTIVE INGREDIENTS: grape flavoring, purified water, sodium benzoate, sorbitol and sucralose.

CLINICAL PHARMACOLOGY

Sodium citrate is absorbed and metabolized to sodium bicarbonate, thus acting as a systemic alkalizer. The effects are essentially those of chlorides before absorption and those of bicarbonates subsequently. Oxidation is virtually complete so that less than 5% of sodium citrate is excreted in the urine unchanged.

INDICATIONS AND USAGE

Sodium citrate and citric acid oral solution, USP is an effective alkalinizing agent. It is useful in those conditions where long-term maintenance of an alkaline urine is desirable, and is of value in the alleviation of chronic metabolic acidosis, such as results from chronic renal insuffi ciency or the syndrome of renal tubular acidosis, especially when the administration of potassium salts is undesirable or contraindicated. This product is also useful for buff ering and neutralizing gastric hydrochloric acid quickly and effectively.
Sodium citrate and citric acid oral solution is concentrated, and when administered after meals and before bedtime, allows one to maintain an alkaline urinary pH around the clock, usually without the necessity of a 2 A.M. dose. This product alkalinizes the urine without producing a systemic alkalosis in the recommended dosage. This product is highly palatable, pleasant tasting, and tolerable, even when administered for long periods.

CONTRAINDICATIONS

Patients on sodium-restricted diets or with severe renal impairment.

PRECAUTIONS

Sodium citrate and citric acid oral solution should be used with caution by patients with low urinary output unless under the supervision of a physician. This product should not be administered concurrently with aluminum-based antacids. Patients should be directed to dilute adequately with water and preferably, to take each dose after meals to avoid saline laxative effect. Sodium salts should be used cautiously in patients with cardiac failure, hypertension, impaired renal function, peripheral and pulmonary edema, and toxemia of pregnancy. Periodic examinations and determinations of serum electrolytes, particularly serum bicarbonate level, should be carried out in those patients with renal disease in order to avoid these complications.

ADVERSE REACTIONS

Sodium citrate and citric acid oral solution is generally well tolerated, without any unpleasant side effects, when given in recommended doses to patients with normal renal function and urinary output. However, as with any alkalinizing agent, caution must be used in certain patients with abnormal renal mechanisms to avoid development of alkalosis, especially in the presence of hypocalcemia.
To report SUSPECTED ADVERSE REACTIONS, contact Kesin Pharma at 1-833-537-4679 or FDA at 1-800-FDA-1088 or www.fda.gov/medwatch.

OVERDOSAGE

Overdosage with sodium salts may cause diarrhea, nausea and vomiting, hypernoia, and convulsions.

DOSAGE AND ADMINISTRATION

Sodium citrate and citric acid oral solution should be taken diluted in water, followed by additional water, if desired. SHAKE WELL BEFORE USING.

For Systemic Alkalization

Usual Adult Dose
2 to 6 teaspoonfuls (10 to 30 mL), diluted in 1 to 3 ounces of water, after meals and at bedtime, or as directed by a physician.
Usual Pediatric Dose
1 to 3 teaspoonfuls (5 to 15 mL), diluted in 1 to 3 ounces of water, after meals and at bedtime, or as directed by a physician. For children under two years of age, use is based on consultation with a physician.

As a neutralizing buffer

3 teaspoonfuls (15 mL), diluted with 15 mL water, taken as a single dose, or as directed by a physician.

HOW SUPPLIED

Sodium Citrate and Citric Acid Oral Solution, USP (colorless, grape flavor) is supplied in the following oral dosage forms:
NDC 81033-017-15: 15 mL unit dose cup
NDC 81033-017-50: Case containing 100 unit-dose cups of 15 mL
NDC 81033-017-30: 30 mL unit dose cup
NDC 81033-017-51: Case containing 100 unit-dose cups of 30 mL

STORAGE

Keep tightly closed. Store at controlled room temperature, 20°C to 25°C (68°F to 77°F). Protect from freezing.

Rx Only
Packaged by:
Kesin Pharma
Oldsmar, Florida 34677
Revised March 2025
PI Rev. 01

PACKAGE LABEL

NDC 81033-017-50

Sodium Citrate and Citric Acid Oral Solution, USP

1.5g/1g per 15mL

Delivers 15mL

Case = 100 UD Cups (Do Not Break Case)

QTY 1

PACKAGE LABEL

NDC 81033-017-51

Sodium Citrate and Citric Acid Oral Solution, USP

3g/2g per 30mL

Delivers 30mL

Case = 100 D Cups (Do Not Break Case)

QTY 1